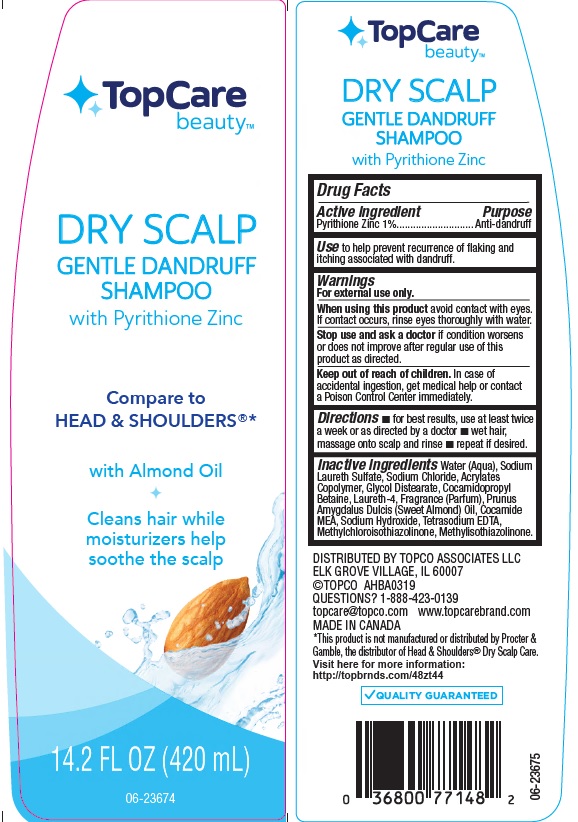 DRUG LABEL: TopCare Dry Scalp Gentle Dandruff
NDC: 36800-796 | Form: SHAMPOO
Manufacturer: Topco Associates LLC
Category: otc | Type: HUMAN OTC DRUG LABEL
Date: 20190927

ACTIVE INGREDIENTS: PYRITHIONE ZINC 10 mg/1 mL
INACTIVE INGREDIENTS: WATER; SODIUM LAURETH SULFATE; SODIUM CHLORIDE; METHACRYLIC ACID - METHYL METHACRYLATE COPOLYMER (1:1); GLYCOL DISTEARATE; COCAMIDOPROPYL BETAINE; LAURETH-4; ALMOND OIL; COCO MONOETHANOLAMIDE; SODIUM HYDROXIDE; EDETATE SODIUM; METHYLCHLOROISOTHIAZOLINONE; METHYLISOTHIAZOLINONE

Drug Facts

Active ingredient

Pyrithione Zinc 1%

Purpose

Antidandruff

Use

to help prevent recurrence of flaking and itching associated with dandruff

Warnings

For external use only

When using this product

avoid contact with eyes. If contact occurs, rinse eyes thoroughly with water

Stop use and ask a doctor if

condition worsens or does not improve after regular use of this product as directed.

Keep out of reach of children.

In case of accidental ingestion, get medical help or contact a Poison Control Center immediately.

Directions

- for best results, use twice a week or as directed by a doctor
- wet hair, massage onto scalp and rinse.
- repeat if desired.

Inactive ingredients

Water (Aqua), Sodium Laureth Sulfate, Sodium Chloride, Acrylates Copolymer, Glycol Distearate, Cocamidopropyl Betaine, Laureth-4, Fragrance (Parfum), Prunus Amygdalus Dulcis (Sweet Almond) Oil, Cocamide MEA, Sodium Hydroxide, Tetrasodium EDTA, Methylchloroisothiazolinone, Methylisothiazolinone.